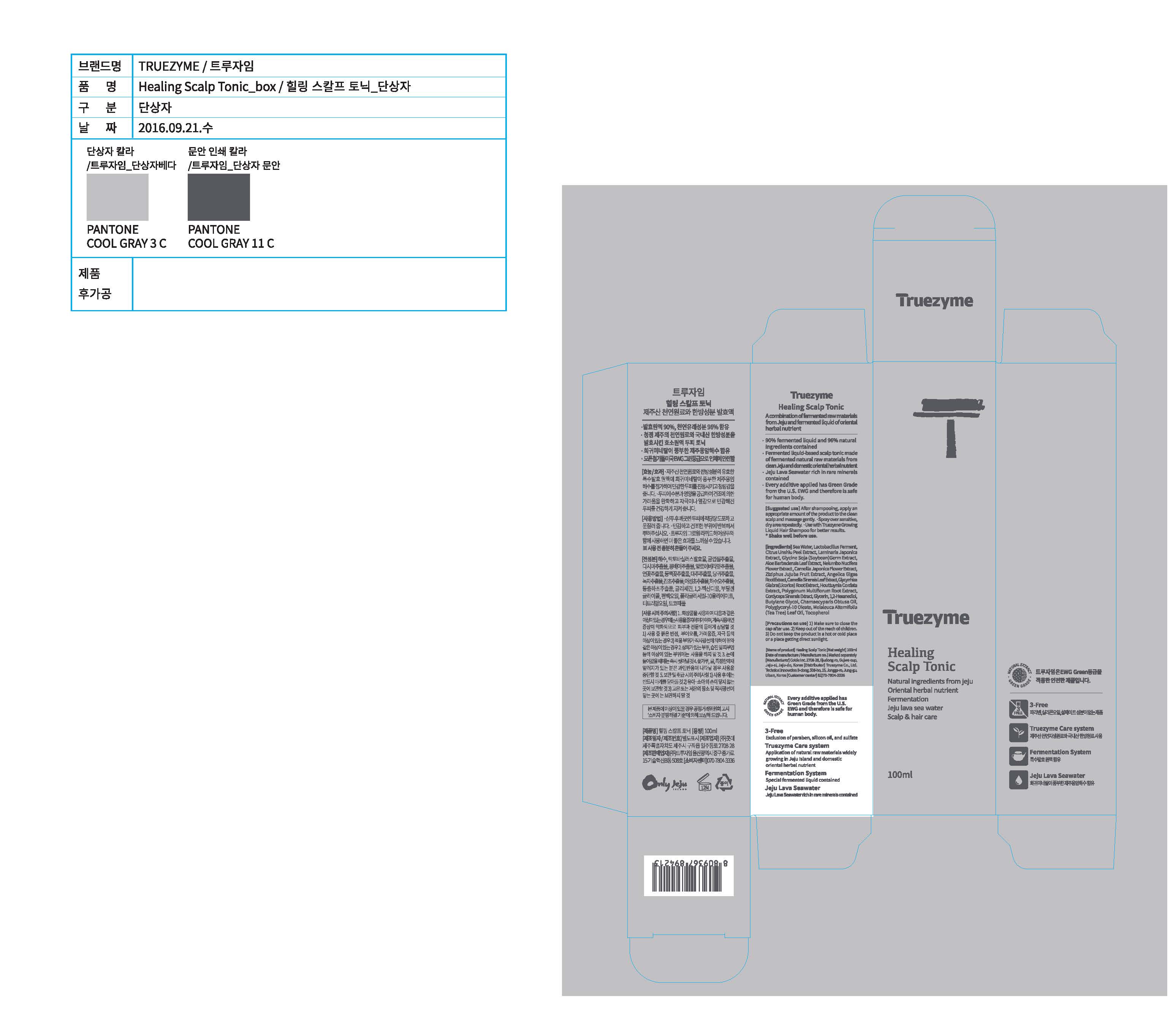 DRUG LABEL: Truezyme Healing Scalp Tonic
NDC: 71076-0005 | Form: LIQUID
Manufacturer: Truezyme Co., Ltd.
Category: otc | Type: HUMAN OTC DRUG LABEL
Date: 20161227

ACTIVE INGREDIENTS: GLYCERIN 5 g/100 mL
INACTIVE INGREDIENTS: CAMELLIA JAPONICA FLOWER; ALOE VERA LEAF; GREEN TEA LEAF

Drug Facts

Active ingredient

Glycerin

Purpose

Nourish the sensitive scalp and also make hair lustrous and strong

DOSAGE AND ADMINISTRATION

For external use only

INDICATIONS AND USAGE

After shampooing, apply an appropriate amount of the product to the clean scalp and massage gently.

- Spray over sensitive, dry area repeatedly.
- Use with Truezyme Growing Liquid Hair Shampoo for better results.

* Shake well before use.

Inactive ingredients:

Camellia Sinensis Leaf Extract, Camellia Japonica Flower Extract, Aloe Barbadensis Leaf Extract, etc.

Keep out of reach of children.

WARNINGS

1. Make sure to close the cap after use.
2. Keep out of the reach of children.
3. Do not keep the product in a hot or cold place or a place getting direct sunlight.